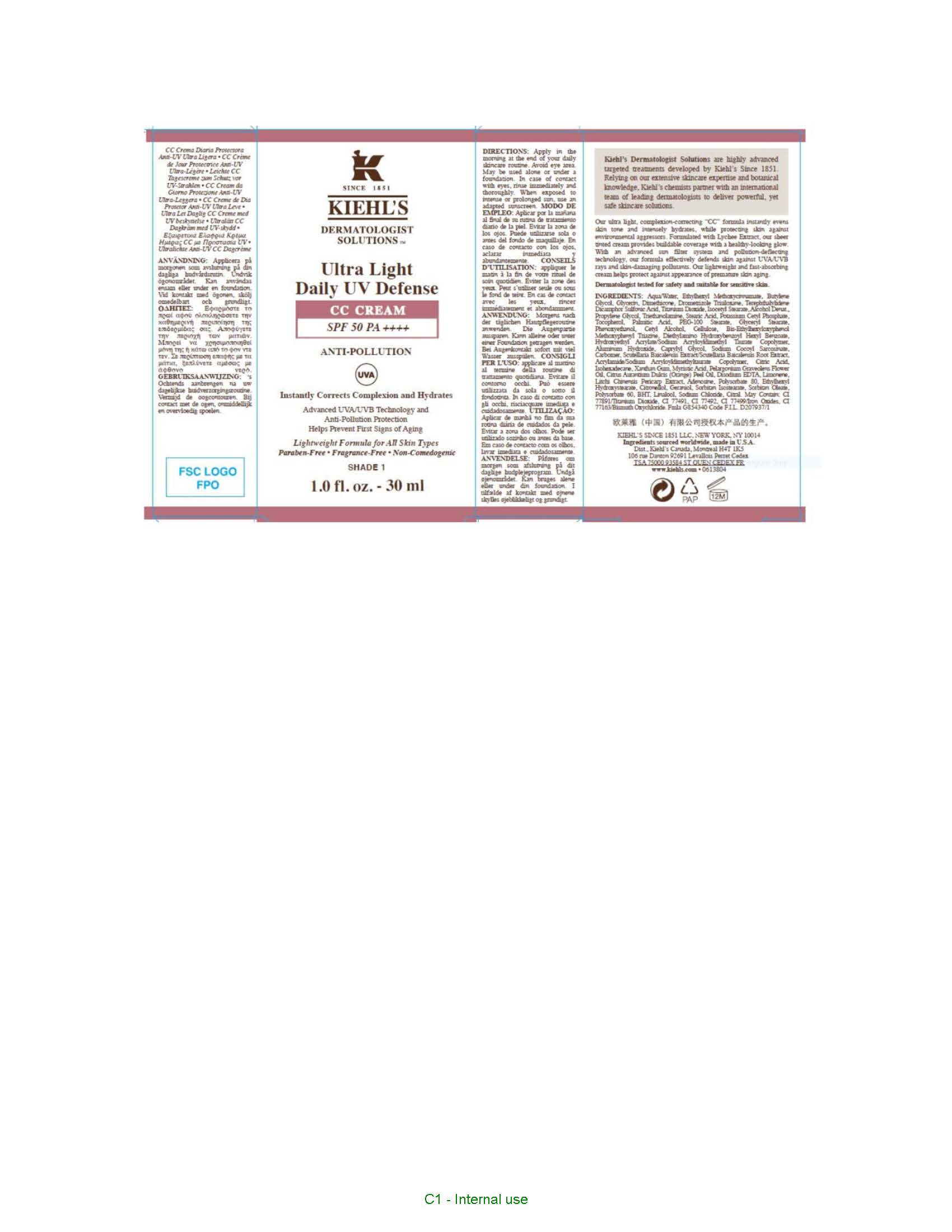 DRUG LABEL: Kiehls Ultra Light Daily UV Defense CC SPF 50 Anti Pollution
NDC: 49967-161 | Form: CREAM
Manufacturer: L'Oreal USA Products Inc
Category: otc | Type: HUMAN OTC DRUG LABEL
Date: 20260107

ACTIVE INGREDIENTS: DROMETRIZOLE TRISILOXANE 40 mg/1 mL; ECAMSULE 120 mg/1 mL; BEMOTRIZINOL 5 mg/1 mL; TITANIUM DIOXIDE 40 mg/1 mL; OCTINOXATE 67.5 mg/1 mL; DIETHYLAMINO HYDROXYBENZOYL HEXYL BENZOATE 5 mg/1 mL
INACTIVE INGREDIENTS: WATER; BUTYLENE GLYCOL; GLYCERIN; DIMETHICONE; ISOCETYL STEARATE; ALCOHOL; PROPYLENE GLYCOL; STEARIC ACID; POTASSIUM CETYL PHOSPHATE; TOCOPHEROL; PEG-100 STEARATE; GLYCERYL MONOSTEARATE; PHENOXYETHANOL; CETYL ALCOHOL; POWDERED CELLULOSE; ALUMINUM HYDROXIDE; CAPRYLYL GLYCOL; SODIUM COCOYL SARCOSINATE; CARBOXYPOLYMETHYLENE; SCUTELLARIA BAICALENSIS ROOT; CITRIC ACID MONOHYDRATE; ISOHEXADECANE; XANTHAN GUM; MYRISTIC ACID; PELARGONIUM GRAVEOLENS FLOWER OIL; ORANGE OIL; EDETATE DISODIUM; ADENOSINE; POLYSORBATE 80; ETHYLHEXYL HYDROXYSTEARATE; SORBITAN ISOSTEARATE; SORBITAN MONOOLEATE; POLYSORBATE 60; BUTYLATED HYDROXYTOLUENE; SODIUM CHLORIDE

Drug Facts

Directions

Apply in the morning at the end of your daily skincare routine. Avoid eye area. May be used alone or under a foundation. In case of contact with eyes, rinse immediately and thoroughly. When exposed to intense ot prolonged sun, use an adapted sunscreen.

Ingredients

Drometrizole Trisiloxane, Terephthalylidene Dicamphor Sulfonic Acid, Bis-ethylhexyloxyphenol methoxyphenyl triazine, Titanium Dioxide, Ethylhexyl Methoxycinnamate, Diethylamino Hydroxybenzoyl Hexyl Benzoate

Ingredients

Aqua/Water, Butylene Glycol, Glycerin, Dimethicone, Isocetyl Stearate, Alcohol Denate., Propylene Glycol, Stearic Acid, Potassium Cetyl Phosphate, Tocopherol, Palmitic Acid, PEG-100 Stearate, Glyceryl Stearate, Phenoxyethanol, Cetyl alcohol, Cellulose, Hydroxyethyl Acrylate/Sodium Acryloyldimethyl Taurate Copolymer, Aluminum Hydroxide, Caprylyl Glycol, Sodium Cocoyl Sarcosinate, Carbomer, Scutellaria Baicalensis Extract/Scutellaria Baicalensis Root Extract, Acrylamide/Sodium Acryloyldimethyltaurate Copolymer, Citric Acid, Isohexadecane, Xanthan Gum, Myristic Acid, Pelargonium Graveolens Flower Oil, Citrus Aurantium Dulcis (Orange) Peel Oil, Disodium EDTA, Litchi Chinensis Pericarp Extract, Adenosine, Polysorbate 80, Ethylhexyl Hydroxystearate, Sorbitan Isostearate, Sorbitan Oleate, Polysorbate 60, BHT, Sodium Chloride. May Contain: CI77891/Titanium Dioxide, CI 77491, CI 77492, CI 77499/Iron Oxides, CI 77163/Bismuth Oxychloride